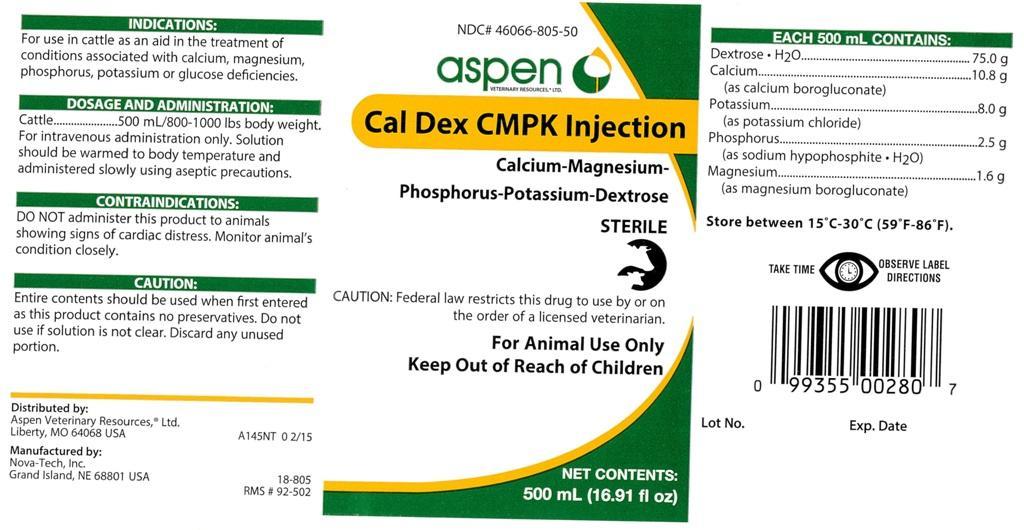 DRUG LABEL: Cal Dex CMPK
NDC: 46066-805 | Form: INJECTION, SOLUTION
Manufacturer: Aspen Veterinary
Category: animal | Type: PRESCRIPTION ANIMAL DRUG LABEL
Date: 20151111

ACTIVE INGREDIENTS: Dextrose monohydrate 75 g/500 mL; Potassium Chloride 8.0 g/500 mL; Calcium Gluconate Monohydrate 10.8 g/500 mL; Phosphorus 2.5 g/500 mL; Magnesium Gluconate 1.6 g/500 mL

Cal Dex CMPK Injection

INDICATIONS:

For use in cattle as an aid in the treatment of
conditions associated with calcium, magnesium,
phosphorus, potassium or glucose deficiencies.

DOSAGE AND ADMINISTRATION:

Cattle ....... 500 mL/800-1000 lbs body weight.
For intravenous administration only. Solution
should be warmed to body temperature and
administered slowly using aseptic precautions.

CONTRAINDICATIONS:

DO NOT administer this product to animals
showing signs of cardiac distress. Monitor animal's
condition closely.

CAUTION:

Entire contents should be used when first entered
as this product contains no preservatives. Do not
use if solution is not clear. Discard any unused
portion.

CAUTION:

Federal law restricts this drug to use by or on
the order of a licensed veterinarian.

VETERINARY INDICATIONS

For Animal Use Only

Keep Out of Reach of Children

INFORMATION FOR OWNERS/CAREGIVERS

NET CONTENTS: 500 mL (16.91 fl oz)

EACH 500 mL CONTAINS:

Dextrose.H2O ........................ 75.0 g
Calcium ................................ 10.8 g
(as calcium borogluconate)
Potassium ............................. 8.0 g
(as potassium chloride)
Phosphorus ........................... 2.5 g
(as sodium hypophosphite.H2O)
Magnesium ............................ 1.6 g
(as magnesium borogluconate)

STORAGE AND HANDLING

Store between 15 degrees C - 30 degrees C (59 degrees F - 86 degrees F).

INFORMATION FOR OWNERS/CAREGIVERS

Calcium-Magnesium-Phosphorus-Potassium-Dextrose

STERILE

Distributed by:Aspen Veterinary Resources,R Ltd.
Liberty, MO 64068 USA A145NT 0 2/15

Manufactured by:
Nova-Tech, Inc.
Grand Island, NE 68801 USA

18-805
RMS # 92-502

Lot No. Exp. Date

WARNINGS AND PRECAUTIONS

TAKE TIME OBSERVE LABEL DIRECTIONS